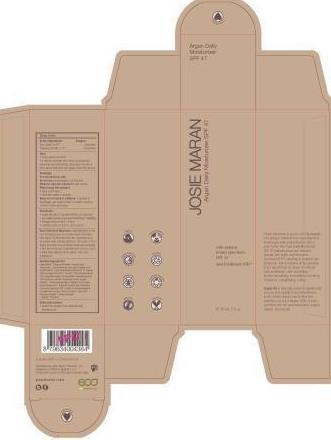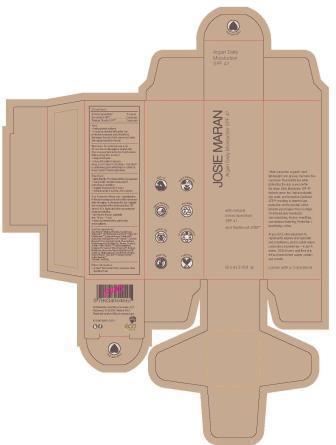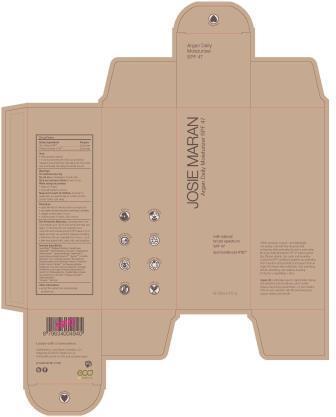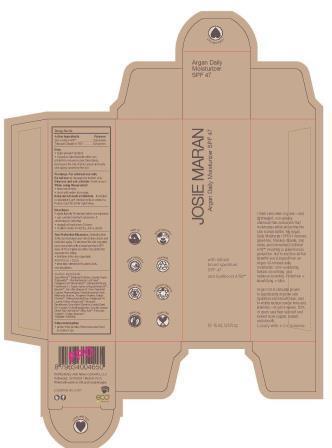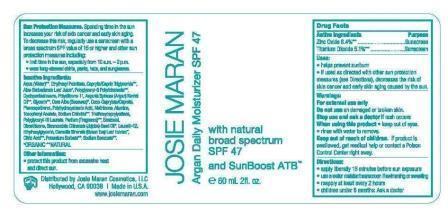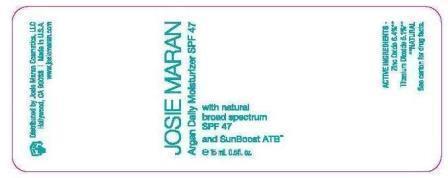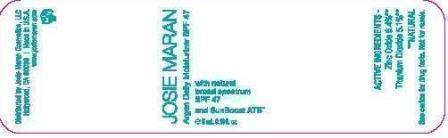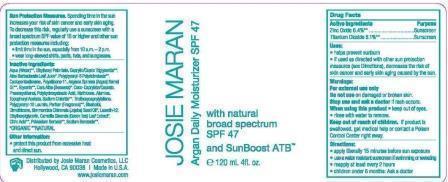 DRUG LABEL: Josie Maran Argan Daily Moisturizer SPF47
NDC: 51514-0332 | Form: LOTION
Manufacturer: Autumn Harp, Inc.
Category: otc | Type: HUMAN OTC DRUG LABEL
Date: 20230114

ACTIVE INGREDIENTS: ZINC OXIDE 6.4 mg/100 mL; TITANIUM DIOXIDE 5.1 mg/100 mL
INACTIVE INGREDIENTS: WATER; CYCLOMETHICONE 5; ETHYLHEXYL PALMITATE; MEDIUM-CHAIN TRIGLYCERIDES; POLYGLYCERYL-6 DIOLEATE; POLYSILICONE-15; ARGAN OIL; GLYCERIN; COCO-CAPRYLATE/CAPRATE; YELLOW WAX; PHENOXYETHANOL; POLYHYDROXYSTEARIC ACID (2300 MW); METHICONE (20 CST); ALUMINUM OXIDE; .ALPHA.-TOCOPHEROL ACETATE; SODIUM CHLORIDE; TRIETHOXYCAPRYLYLSILANE; POLYGLYCERYL-10 LAURATE; APRICOT; LEVOMENOL; JOJOBA OIL; DIMETHICONE; ALOE VERA LEAF; LAURETH-12; LINALOOL, (+/-)-; ETHYLHEXYLGLYCERIN; LIMONENE, (+/-)-; GREEN TEA LEAF; .ALPHA.-AMYLCINNAMALDEHYDE; POTASSIUM SORBATE; SODIUM BENZOATE; CITRIC ACID MONOHYDRATE

Josie Maran Argan Daily Moisturizer SPF47

Drug Facts

Active Ingredients

Zinc Oxide 6.4%**

Titanium Dioxide 5.1%**

Purpose

Sunscreen

Sunscreen

Uses

· helps prevent sunburn

· if used as directed with other sun protection measures (see Directions), decreases the risk of skin cancer and early skin aging caused by the sun.

Warnings

For external use only

Do not use on damaged or broken skin.

Stop use and ask a doctor if rash occurs.

When using this product

· keep out of eyes

· rinse with water to remove

Keep out of reach of children. If product is swallowed, get medical help or contact a Poison Control Center right away.

Directions:

• apply liberally 15 minutes before sun exposure

• use a water resistant sunscreen if swimming or sweating

• reapply at least every 2 hours

• children under 6 months: Ask a doctor

WHEN USING

Sun Protection Measures. Spending time in the sun increases your risk of skin cancer and early skin aging. To decrease the risk, regularly use a sunscreen with a Broad Spectrum SPF value of 15 or higher and other sun protection measures including:

• Limit time in the sun, especially from 10am - 2pm.

• Wear long-sleeve shirts, pants, hats, and sunglasses

Inactive Ingredients:

Aqua (Water)**, Ethylhexyl Palmitate, Caprylic/Capric

Triglyceride**, Aloe Barbadensis Leaf Juice*, Polyglyceryl-6

Polyricinoleate**, Cyclopentasiloxane, Polysilicone-11,

Argania Spinosa (Argan) Kernel Oil**, Glycerin**, Cera Alba

(Beeswax)*, Coco-Caprylate/Caprate, Phenoxyethanol,

Polyhydroxystearic Acid, Methicone, Alumina, Tocopheryl

Acetate, Sodium Chloride**, Triethoxycaprylylsilane,

Polyglyceryl-10 Laurate, Parfum (Fragrance)**, Bisabolol,

Dimethicone, Simmondsia Chinensis (Jojoba) Seed Oil*,

Laureth-12, Ethylhexylglycerin, Camellia Sinensis (Green

Tea) Leaf Extract*, Citric Acid**, Potassium Sorbate**,

Sodium Benzoate**.

*ORGANIC **NATURAL

Other Information:

· Protect this product from excessive heat and direct sun.

DOSAGE AND ADMINISTRATION

Apply as needed

Keep out of reach of children

WARNINGS

For external use only

Do not use on damaged or broken skin

When using this product, keep out of eyes

Principle Display Panel

\ Image Components